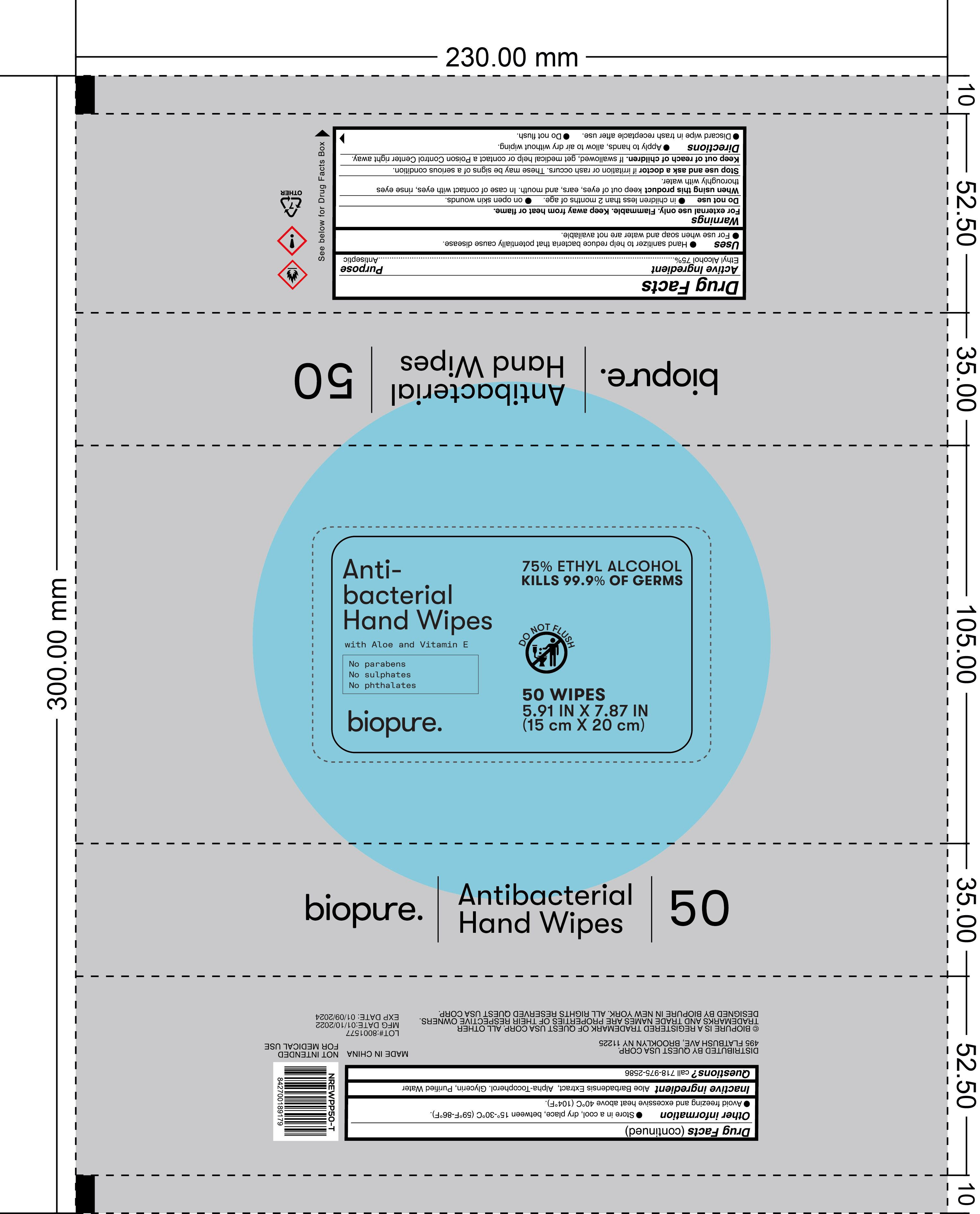 DRUG LABEL: BIOPURE 50CT ANTIBACTERIAL HAND WIPES
NDC: 79866-020 | Form: CLOTH
Manufacturer: Osike Cosmetics co., Ltd
Category: otc | Type: HUMAN OTC DRUG LABEL
Date: 20220120

ACTIVE INGREDIENTS: ALCOHOL 75 mL/100 mL
INACTIVE INGREDIENTS: ALPHA-TOCOPHEROL; GLYCERIN; ALOE VERA WHOLE; WATER

79866-020

ACTIVE INGREDIENT

Ethyl Alcohol 75%

PURPOSE

Antiseptic

Uses

●Hand sanitizer to help reduce bacteria that potentially cause disease.

●For use when soap and water are not available.

WARNINGS

For external use only. Flammable. Keep away from heat or flame.

DO NOT USE

●in children less than 2 months of age.

●on open skin wounds

WHEN USING

keep out of eyes, ears, and mouth. In case of contact with eyes, rinse eyes thoroughly with water.

STOP USE

irritation or rash occurs. These may be signs of a serious condition.

KEEP OUT OF REACH OF CHILDREN

If swallowed. get medical help or contact a Poison Control Center right away.

Directions

●Apply to hands, allow to air dry without wiping.

●Discard wipe in trash receptacle after use.

● Do not flush.

Other information

●Store in a cool, dry place, between 15°C-30°C（59°F-86°F）

●Avoid freezing and excessive heat above 40°C（104°F）

INACTIVE INGREDIENT

Aloe Barbadensis Extract, Alpha-Tocopherol, Glycerin, Purified Water